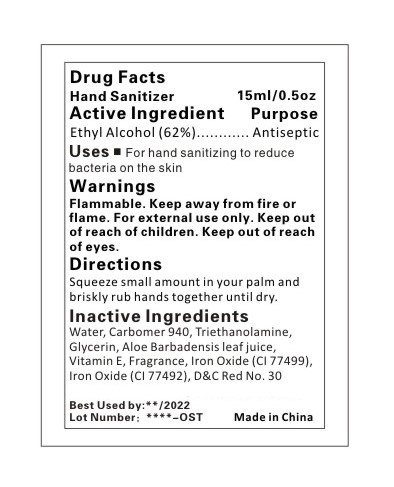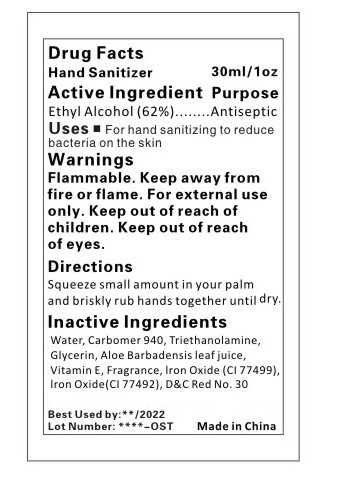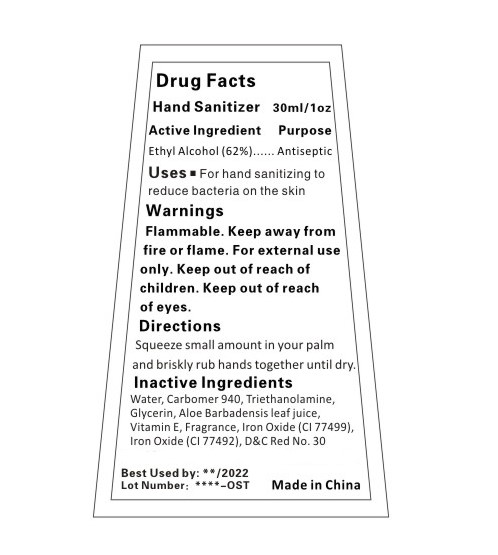 DRUG LABEL: HAND SANITIZER
NDC: 47993-300 | Form: GEL
Manufacturer: NINGBO JIANGBEI OCEAN STAR TRADING CO.,LTD
Category: otc | Type: HUMAN OTC DRUG LABEL
Date: 20201105

ACTIVE INGREDIENTS: ALCOHOL 62 g/112 mL
INACTIVE INGREDIENTS: WATER; CARBOMER 940; TRIETHANOLAMINE BENZOATE; GLYCERIN; ALOE VERA LEAF; TOCOPHEROL; FERROSOFERRIC OXIDE; FERRIC OXIDE YELLOW; D&C RED NO. 30

47993-300

Active ingredients

Ethyl Alcohol 62%

PURPOSE

Antiseptic

Uses：

For hand sanitizing to reduce bacteria on the skin.

Warnings:

Flammable. Keep away from fire or flame.

For external use only.

Keep out of reach of children.

WHEN USING

Keep out of reach of eyes.

Directions:

Squeeze small amount in your palm and briskly rub hands together until dry.

Inactive Ingredients:

Water,Carbomer 940,Triethanolamine,Glycerin,Aloe Barbadensis leaf juice,Vitamin E,Fragrance,Iron Oxide(CI 77499),Iron Oxide(CI 77492),D&C Red No.30